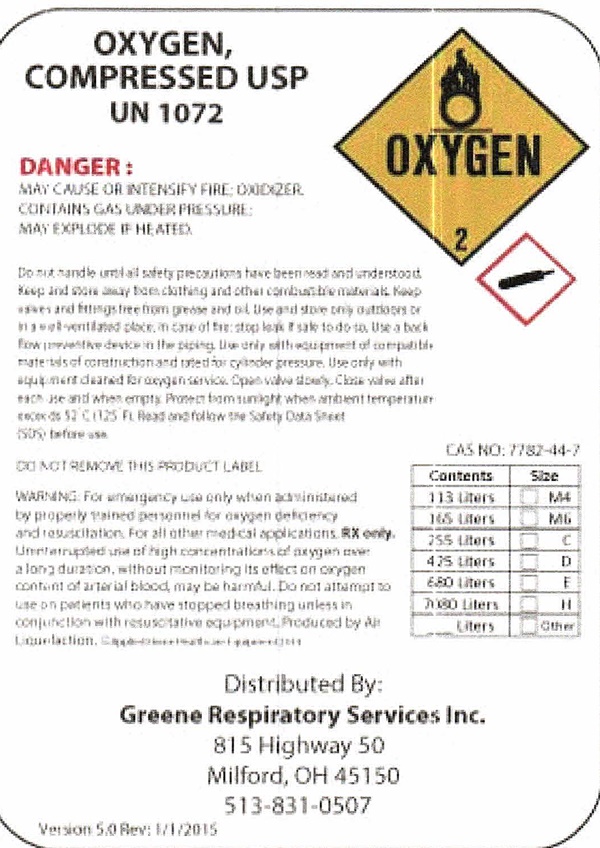 DRUG LABEL: OXYGEN
NDC: 64140-101 | Form: GAS
Manufacturer: Greene Respiratory Services, Inc
Category: prescription | Type: HUMAN PRESCRIPTION DRUG LABEL
Date: 20251125

ACTIVE INGREDIENTS: OXYGEN 99 L/100 L

Oxygen Compressed - Product Label

OXYGEN,

COMPRESSED U.S.P.

UN 1072

OXYGEN 2

DANGER:
MAY CAUSE OR INTENSIFY FIRE; OXIDIZER
CONTAINS GAS UNDER PRESSURE;
MAY EXPLODE IF HEATED

Do not handle until all safety precautions have been read and understood. Keep and store away from clothing and other combustible materials. Keep
valves and fittings free from grease and oil. Use and store only outdoors or in a well-ventilated place. In case of fire: stop leak if safe to do so. Use a back flow preventive device in the piping. Use only with equipment of compatible materials of construction and rated for cylinder pressure. Use only with equipment cleaned for oxygen service. Open valve slowly. Close valve after each use and when empty. Protect from sunlight when ambient temperature exceeds 52°C (125°F). Read and follow the Safety Data Sheet (SDS) before use.

DO NOT REMOVE THIS PRODUCT LABEL

WARNING: For emergency use only when administered by properly trained personnel for oxygen deficiency and resusciation. For all other medical applications, RX only. Uninterrupted use of high concentrations of oxygen over a long duration, without monitoring its effect on oxygen content of arterial blood, may be harmful. Do not attempt to use on patients who have stopped breathing unless in conjunction with resuscitative equippment. Produced by Air Liquiefaction.

CAS NO: 7782-44-7

Contents | Size
113 Liters | M4
165 Liters | M6
255 Liters | C
425 Liters | D
680 Liters | E
7080 Liters | H
____ Liters | Other

Distributed By:

Greene Respiratory Services Inc.
815 Highway 50
Milford,OH 45150
513-831-9507

Version 5.0 Rev: 1/1/2015

res